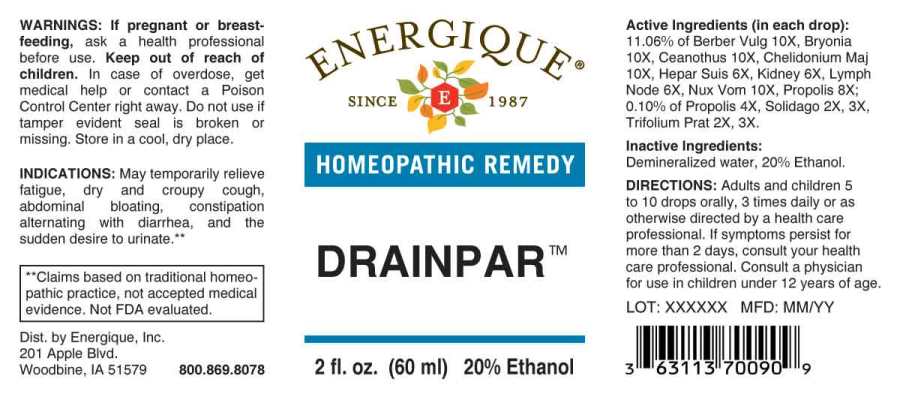 DRUG LABEL: Drainpar
NDC: 44911-0634 | Form: LIQUID
Manufacturer: Energique, Inc.
Category: homeopathic | Type: HUMAN OTC DRUG LABEL
Date: 20241024

ACTIVE INGREDIENTS: SOLIDAGO VIRGAUREA FLOWERING TOP 2 [hp_X]/1 mL; TRIFOLIUM PRATENSE FLOWER 2 [hp_X]/1 mL; PROPOLIS WAX 4 [hp_X]/1 mL; PORK LIVER 6 [hp_X]/1 mL; PORK KIDNEY 6 [hp_X]/1 mL; SUS SCROFA LYMPH 6 [hp_X]/1 mL; BERBERIS VULGARIS ROOT BARK 10 [hp_X]/1 mL; BRYONIA ALBA ROOT 10 [hp_X]/1 mL; CEANOTHUS AMERICANUS LEAF 10 [hp_X]/1 mL; CHELIDONIUM MAJUS WHOLE 10 [hp_X]/1 mL; STRYCHNOS NUX-VOMICA SEED 10 [hp_X]/1 mL
INACTIVE INGREDIENTS: WATER; ALCOHOL

DRUG FACTS:

ACTIVE INGREDIENTS:

(in each drop): 11.06% of Berberis Vulgaris 10X, Bryonia (Alba) 10X, Ceanothus Americanus 10X, Chelidonium Majus 10X, Hepar Suis 6X, Kidney (Suis) 6X, Lymph Node (Suis) 6X, Nux Vomica 10X, Propolis 8X; 0.10% of Propolis 4X, Solidago Virgaurea 2X, 3X, Trifolium Pratense 2X, 3X.

INDICATIONS:

May temporarily relieve fatigue, dry and croupy cough, abdominal bloating, constipation alternating with diarrhea, and the sudden desire to urinate.**

**Claims based on traditional homeopathic practice, not accepted medical evidence. Not FDA evaluated.

WARNINGS:

If pregnant or breast-feeding, ask a health professional before use.

Keep out of reach of children. In case of overdose, get medical help or contact a Poison Control Center right away.

Do not use if tamper evident seal is broken or missing. Store in a cool, dry place.

Keep out of reach of children. In case of overdose, get medical help or contact a Poison Control Center right away.

DIRECTIONS:

Adults and children 5 to 10 drops orally, 3 times daily or as otherwise directed by a health care professional. If symptoms persist for more than 2 days, consult your health care professional. Consult a physician for use in children under 12 years of age.

INDICATIONS:

May temporarily relieve fatigue, dry and croupy cough, abdominal bloating, constipation alternating with diarrhea, and the sudden desire to urinate.**

**Claims based on traditional homeopathic practice, not accepted medical evidence. Not FDA evaluated.

INACTIVE INGREDIENTS:

Demineralized water, 20% Ethanol

QUESTIONS:

Dist. by Energique, Inc.

201 Apple Blvd

Woodbine, IA 51579 800-869-8078

PACKAGE LABEL DISPLAY:

ENERGIQUE

SINCE 1987

HOMEOPATHIC REMEDY

DRAINPAR

2 fl. oz. (60 ml)